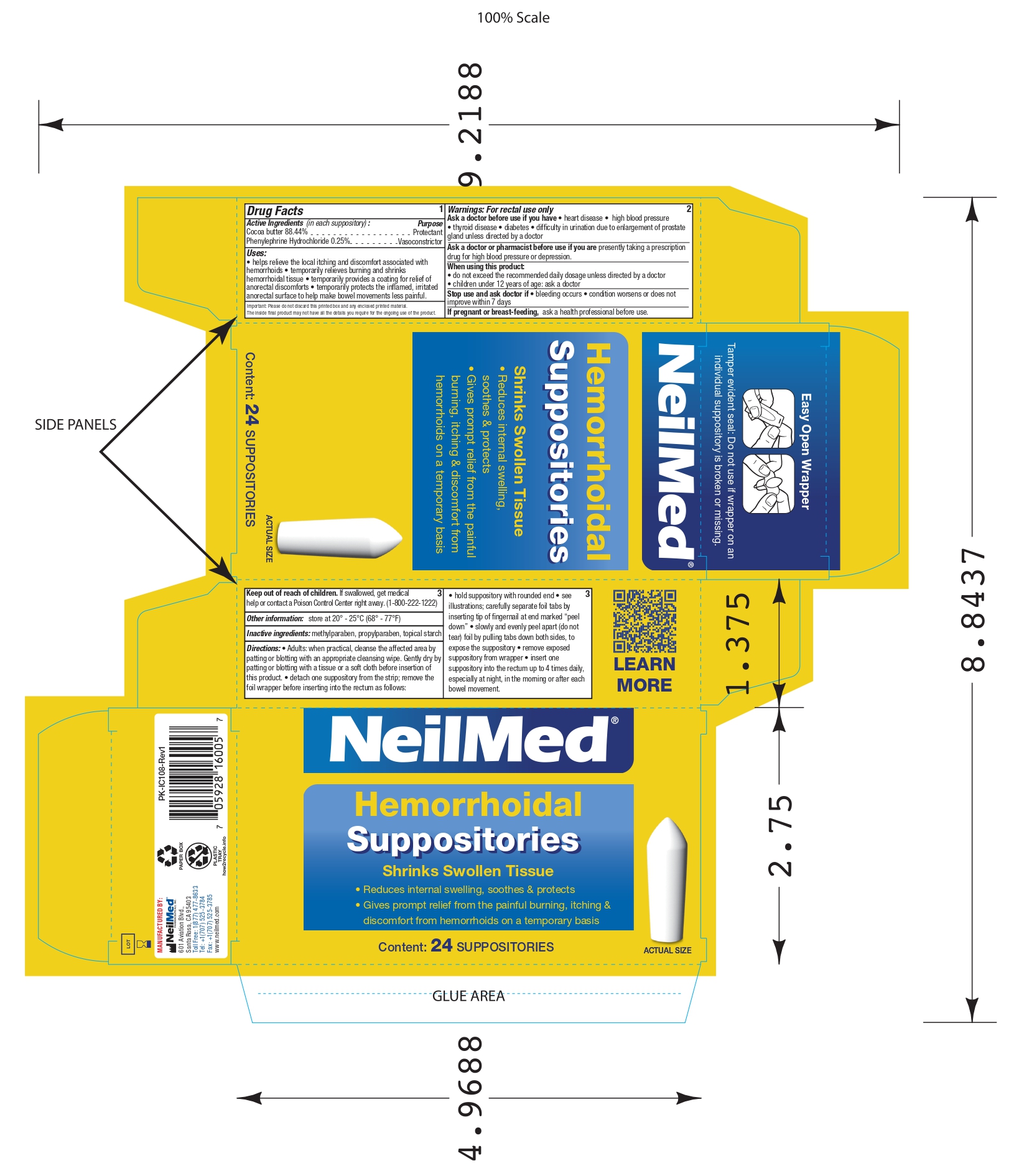 DRUG LABEL: Hemorrhoidal cocoa butter
NDC: 13709-323 | Form: SUPPOSITORY
Manufacturer: NeilMed Pharmaceuticals Inc.
Category: otc | Type: HUMAN OTC DRUG LABEL
Date: 20250117

ACTIVE INGREDIENTS: PHENYLEPHRINE HYDROCHLORIDE 2.5 mg/1 g; COCOA BUTTER 884.4 mg/1 g
INACTIVE INGREDIENTS: METHYLPARABEN; MODIFIED CORN STARCH (1-OCTENYL SUCCINIC ANHYDRIDE); PROPYLPARABEN

NeilMed Hemorrhoidal Suppositories 24count

Drug Facts : Active Ingredients (in each suppository) :

Cocoa butter 88.44%

Phenylephrine Hydrochloride 0.25%

Purpose

Protectant

Vasoconstrictor

Uses:

• helps relieve the local itching and discomfort associated with hemorrhoids • temporarily relieves burning and shrinks hemorrhoidal tissue • temporarily provides a coating for relief of anorectal discomforts • temporarily protects the inflamed, irritatedanorectal surface to help make bowel movements less painful.

Warnings:

For rectal use only

Ask a doctor before use if you have

• heart disease • high blood pressure • thyroid disease • diabetes • difficulty in urination due to enlargement of prostate gland unless directed by a doctor

Ask a doctor or pharmacist before use if you are presently taking a prescription drug for high blood pressure or depression.

When using this product:

• do not exceed the recommended daily dosage unless directed by a doctor
• children under 12 years of age: ask a doctor

Stop use and ask doctor if

• bleeding occurs • condition worsens or does not improve within 7 days

If pregnant or breast-feeding,

ask a health professional before use.

Keep out of reach of children.

If swallowed, get medical
help or contact a Poison Control Center right away. (1-800-222-1222)

Other information:

store at 20° - 25°C (68° - 77°F)

Inactive ingredients:

methylparaben, propylparaben, topical starch

Directions:

• Adults: when practical, cleanse the affected area by patting or blotting with an appropriate cleansing wipe. Gently dry by patting or blotting with a tissue or a soft cloth before insertion of this product. • detach one suppository from the strip; remove the foil wrapper before inserting into the rectum as follows:

• hold suppository with rounded end • see illustrations; carefully separate foil tabs by inserting tip of fingernail at end marked “peel
down” • slowly and evenly peel apart (do not tear) foil by pulling tabs down both sides, to expose the suppository • remove exposed
suppository from wrapper • insert one suppository into the rectum up to 4 times daily, especially at night, in the morning or after each
bowel movement.

INTENDED USE OF THE DEVICE

Shrinks Swollen Tissue
• Reduces internal swelling, soothes & protects
• Gives prompt relief from the painful burning, itching & discomfort from hemorrhoids on a temporary basis